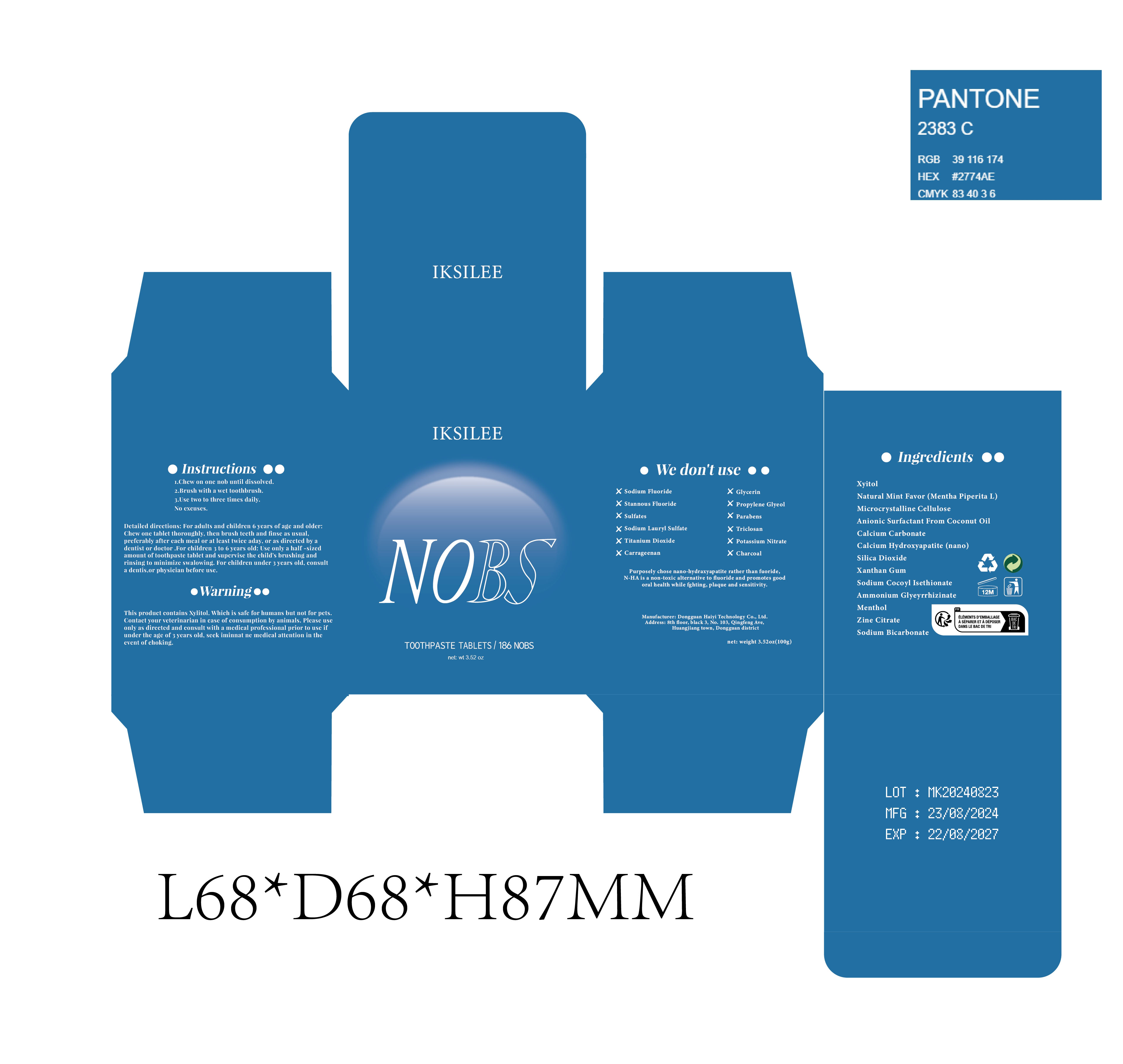 DRUG LABEL: Teeth Cleaning
NDC: 84732-026 | Form: TABLET, CHEWABLE
Manufacturer: Dongguan Haiyi Technology Co.,Ltd.
Category: otc | Type: HUMAN OTC DRUG LABEL
Date: 20240929

ACTIVE INGREDIENTS: XYLITOL 1 mg/100 g; MENTHOL 1 mg/100 g
INACTIVE INGREDIENTS: ZINC CITRATE; AMMONIUM GLYCYRRHIZINATE TRIHYDRATE; SODIUM BICARBONATE; MINT; XANTHAN GUM; TRIBASIC CALCIUM PHOSPHATE; CALCIUM CARBONATE; MICROCRYSTALLINE CELLULOSE; SODIUM COCOYL ISETHIONATE; SILICON DIOXIDE

Active ingredient

Xylitol

Calcium Carbonate

Calcium Hydroxyapatite

Ammonium Glycyrrhizinate

Menthol

Zinc Citrate

Sodium Bicarbonate

Inactive ingredient

Sodium Cocoyl Isethionate

Natural Mint Flavor (Mentha Piperita L)

Microcrystalline Cellulose

Silicon Dioxide

Xanthan Gum

Purpose section

1.Chew on one nob until dissolved.
2.Brush with a wet toothbrush.
3.Use two to three times daily.
No excuses.

Warning

This produet contains Xylitol, Which is safe for humans but not for pets.Contact your veterinarian in case of consumption by animals, Please useonly as direeted and consult with a medical professional prior to use ifunder the age of 3 years old, seek iminnat ne medical attention in the event of choking.

stop use

1.Allergic reaction: If skin redness, itching or other allergic symptoms occur, stop using immediately and consult a doctor.
2. Oral irritation: If irritation or discomfort in the mouth or throat occurs after use, stop using.
3. Oral ulcers or wounds: If there are ulcers, wounds or other conditions in the mouth, and you feel uncomfortable after use, it is recommended to stop using and consult a doctor. Use by children: If swallowed by mistake or used by children, please stop using immediately and seek medical help

not use

Not suitable for use by pregnantor breast feeding people.

OUT OF CHILDREN

as directed by adentist or doctor .For children 3 to 6 vears old: Use only a half -sizedamount of toothpaste tablet and supervise the child's brushing andrinsing to minimize swalowing, For children under 3 years old, consulta dentis,or physician before use.

HOW TO USE

For adults and children 6 years of age and older:Chew one tablet thoroughly, then brush teeth and finse as usual.preferably after each meal or at least twice aday

Dosage

Chew one tablet carefully, then brush and rinse your mouth as usual, preferably after each meal or at least twice daily, or as directed by your dentist or physician.